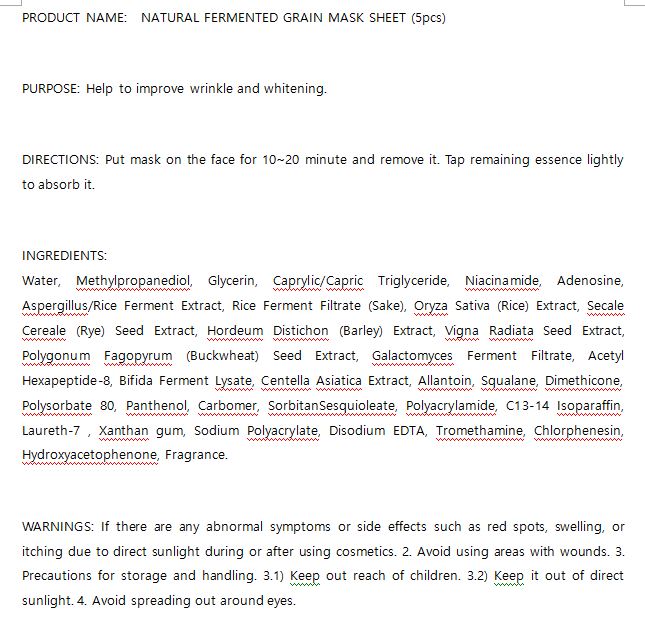 DRUG LABEL: W.SKIN NATURAL FERMENTED GRAIN MASK SHEET
NDC: 74997-0025 | Form: LIQUID
Manufacturer: J&J COMPANY
Category: otc | Type: HUMAN OTC DRUG LABEL
Date: 20210508

ACTIVE INGREDIENTS: CENTELLA ASIATICA 0.01 g/100 g
INACTIVE INGREDIENTS: GLYCERIN; WATER

J&J COMPANY - STOP-AGING PEPTIDE TONER

ACTIVE INGREDIENT

Centella Asiatica Extract

INACTIVE INGREDIENT

Water, Methylpropanediol, Glycerin, Caprylic/Capric Triglyceride, Niacinamide, Adenosine, Aspergillus/Rice Ferment Extract, Rice Ferment Filtrate (Sake), Oryza Sativa (Rice) Extract, Secale Cereale (Rye) Seed Extract, Hordeum Distichon (Barley) Extract, Vigna Radiata Seed Extract, Polygonum Fagopyrum (Buckwheat) Seed Extract, Galactomyces Ferment Filtrate, Acetyl Hexapeptide-8, Bifida Ferment Lysate, Centella Asiatica Extract, Allantoin, Squalane, Dimethicone, Polysorbate 80, Panthenol, Carbomer, SorbitanSesquioleate, Polyacrylamide, C13-14 Isoparaffin, Laureth-7 , Xanthan gum, Sodium Polyacrylate, Disodium EDTA, Tromethamine, Chlorphenesin, Hydroxyacetophenone, Fragrance.

PURPOSE

Help to improve wrinkle and whitening

keep out of reach of the children

INDICATIONS AND USAGE

Put mask on the face for 10~20 minute and remove it. Tap remaining essence lightly to absorb it.

WARNINGS

If there are any abnormal symptoms or side effects such as red spots, swelling, or itching due to direct sunlight during or after using cosmetics. 2. Avoid using areas with wounds. 3. Precautions for storage and handling. 3.1) Keep out reach of children. 3.2) Keep it out of direct sunlight.

DOSAGE AND ADMINISTRATION

for external use only